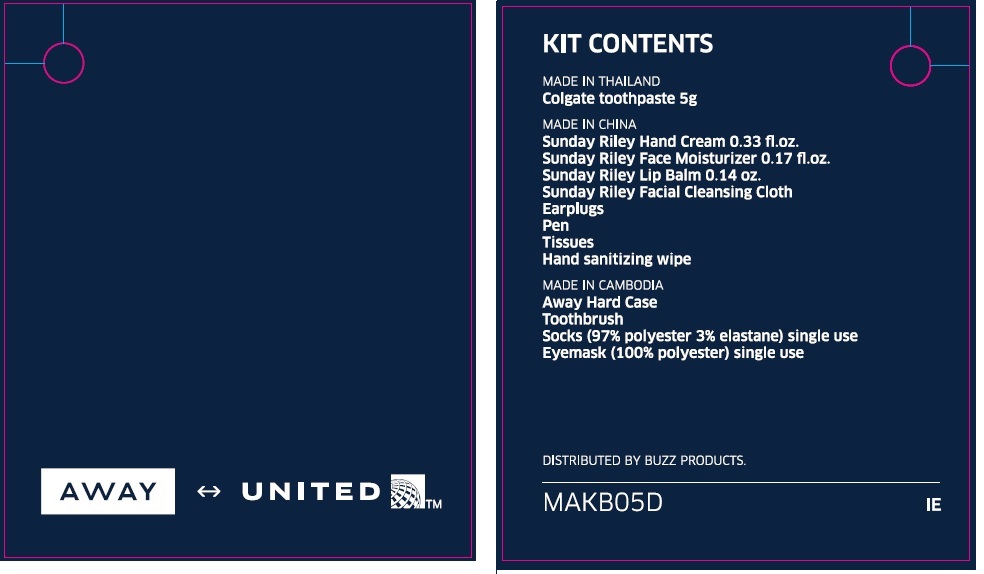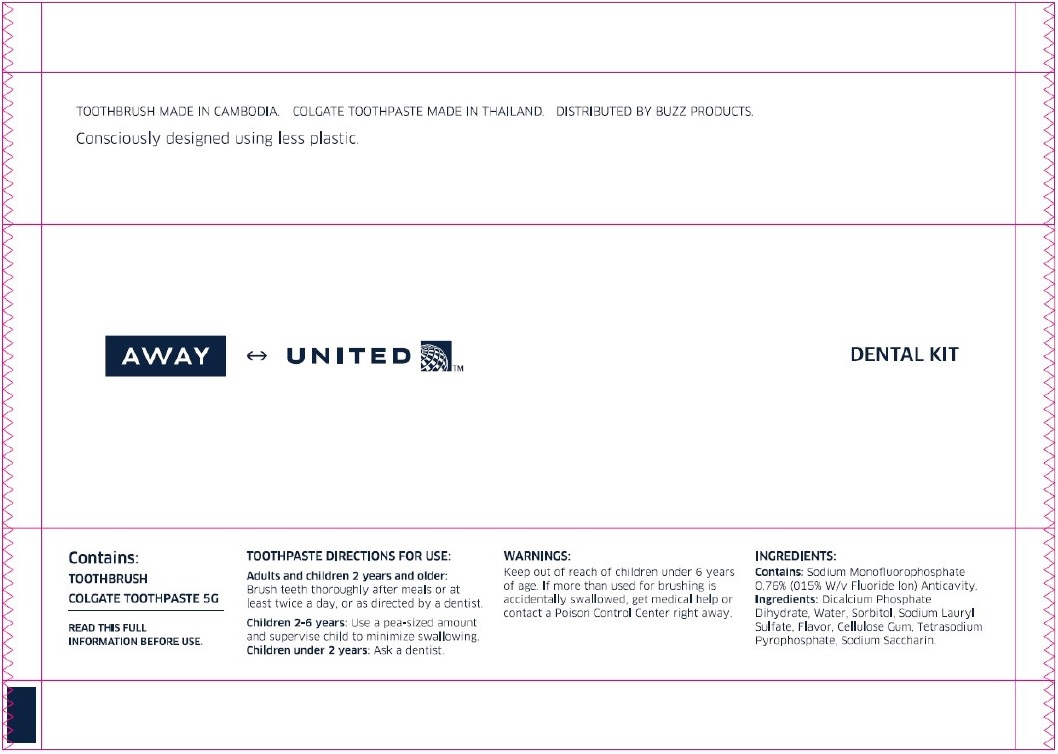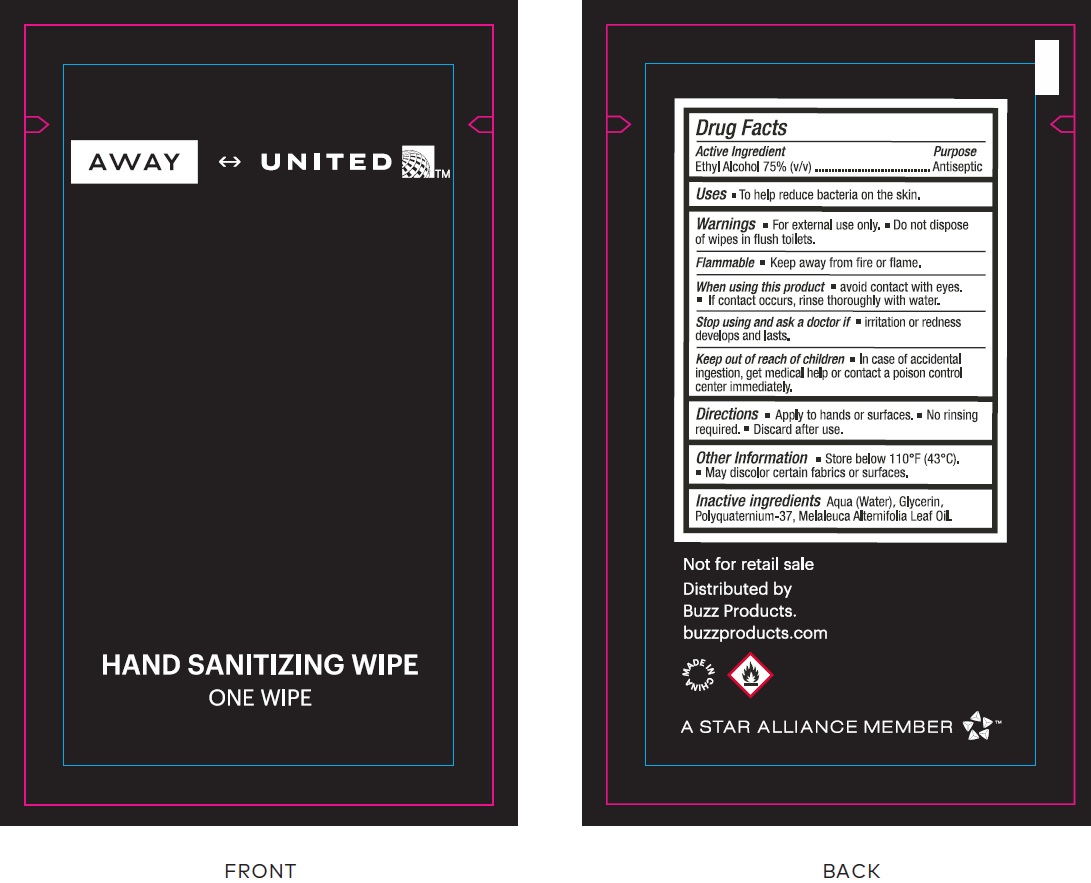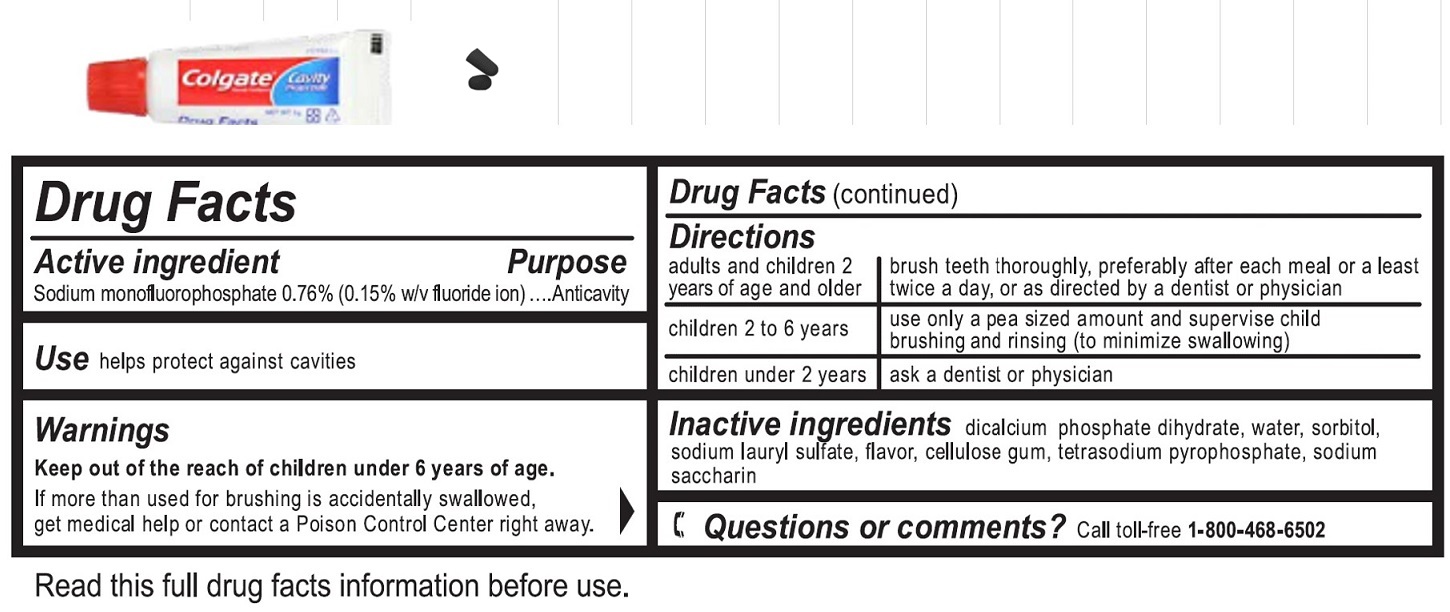 DRUG LABEL: United Airlines Polaris Kit
NDC: 69491-036 | Form: KIT | Route: DENTAL
Manufacturer: Buzz Export Services Pty Ltd (Buzz Products)
Category: otc | Type: HUMAN OTC DRUG LABEL
Date: 20231221

ACTIVE INGREDIENTS: SODIUM MONOFLUOROPHOSPHATE 7.6 mg/1 g; ALCOHOL 75 mL/100 mL
INACTIVE INGREDIENTS: DIBASIC CALCIUM PHOSPHATE DIHYDRATE; WATER; SORBITOL; SODIUM LAURYL SULFATE; METHYL SALICYLATE; CARBOXYMETHYLCELLULOSE SODIUM, UNSPECIFIED; SODIUM PYROPHOSPHATE; SACCHARIN SODIUM; WATER; GLYCERIN; TEA TREE OIL

United Airlines Polaris Kit

Active ingredient

Sodium monofluorophosphate 0.76% (0.15% w/v fluoride ion)

Purpose

Anticavity

Use

helps protect against cavities

Warnings

Keep out of the reach of children under 6 years of age.

If more than used for brushing is accidentally swallowed, get medical help or contact a Poison Control Center right away.

Directions

adults and children 2 years of age and older | brush teeth thoroughly, preferably after each meal or at least twice a day, or as directed by a dentist or physician
children 2 to 6 years | use only a pea sized amount and supervise child's brushing and rinsing (to minimize swallowing)
children under 2 years | ask a dentist or physician

Inactive ingredients

dicalcium phosphate dihydrate, water, sorbitol, sodium lauryl sulfate, flavor, cellulose gum, tetrasodium pyrophosphate, sodium saccharin

Questions or comments?

Call to-free 1-800-468-6502

Active Ingredient

Ethyl Alcohol 75% (v/v)

Purpose

Antiseptic

Uses

- To help reduce bacteria on the skin.

Warnings

- For external use only.
- Do not dispose of wipes in flush toilets.

- Keep away from fire or flame.

Flammable

When using this product

- avoid contact with eyes.
- If contact occurs, rinse thoroughly with water.

Stop using and ask a doctor if

- irritation or redness develops and lasts.

Keep out of reach of children

- In case of accidental ingestion, get medical help or contact a poison control center immediately.

Directions

- Appyl to hands or surface.
- No rinsing required.
- Discard after use.

Other Information

- Store below 110°F (43°C).
- May discolor certain fabrics or surfaces.

Inactive ingredients

Aqua (Water), Glycerin, Polyquaternium-37, Melaleuca Alternifolia Leaf Oil.